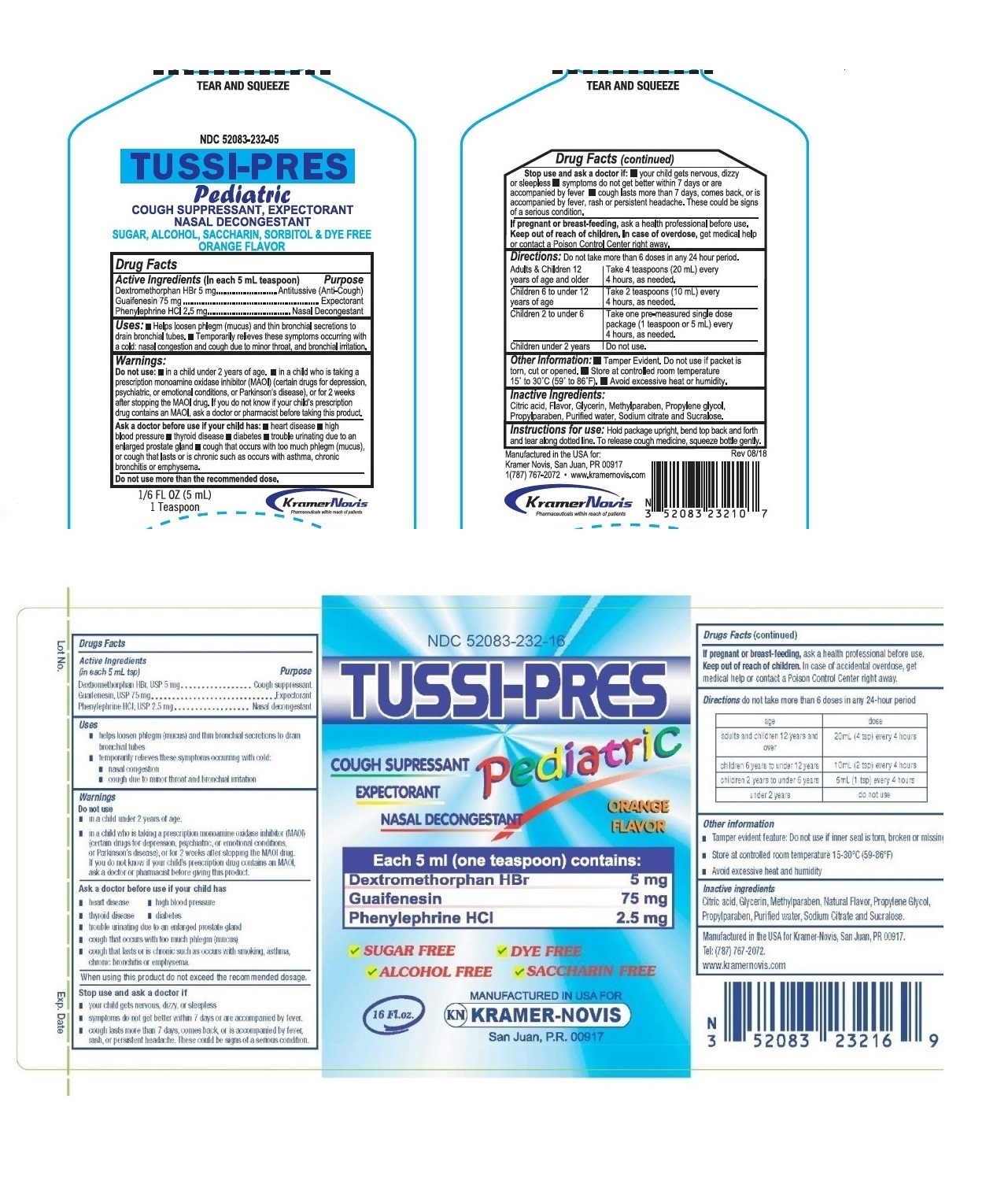 DRUG LABEL: TUSSI PRES PEDIATRIC
NDC: 52083-232 | Form: SYRUP
Manufacturer: KRAMER NOVIS
Category: otc | Type: HUMAN OTC DRUG LABEL
Date: 20251112

ACTIVE INGREDIENTS: GUAIFENESIN 75 mg/5 mL; PHENYLEPHRINE HYDROCHLORIDE 2.5 mg/5 mL; DEXTROMETHORPHAN HYDROBROMIDE 5 mg/5 mL
INACTIVE INGREDIENTS: CITRIC ACID MONOHYDRATE; GLYCERIN; METHYLPARABEN; PROPYLENE GLYCOL; PROPYLPARABEN; WATER; SODIUM CITRATE, UNSPECIFIED FORM; SUCRALOSE

TUSSI PRES PEDIATRIC

Drug Facts

Active Ingredients (In each 5 mL teaspoon)

Dextromethorphan HBr 5 mg

Guaifenesin 75 mg

Phenylephrine HCl 2.5 mg

Purpose

Antitussive (Anti-Cough)

Expectorant

Nasal Decongestant

Uses:

• Helps loosen phlegm (mucus) and thin bronchial secretions to drain bronchial tubes.

• Temporarily relieves these symptoms occurring with a cold: nasal congestion and cough due to minor throat and bronchial irritation.

Warnings:

Do not use: • in a child under 2 years of age. • in a child who is taking a prescription monoamine oxidase inhibitor (MAOI) (certain drugs for depression, psychiatric, or emotional conditions, or Parkinson's disease) or for 2 weeks after stopping the MAOI drug. If you do not know if your child's prescription drug contains an MAOI, ask a doctor or pharmacist before taking this product.

Ask a doctor before use if your child has:

• heart disease • high blood pressure • thyroid disease • diabetes • trouble urinating due to an enlarged prostate gland • cough that occurs with too much phlegm (mucus), or cough that lasts or is chronic such as occurs with asthma, chronic bronchitis or emphysema.

Do not use more than the recommended dose.

Stop use and ask a doctor if: • your child gets nervous, dizzy or sleepless • symptoms do not get better within 7 days or are accompanied by fever • cough lasts more than 7 days, comes back, or is accompanied by fever, rash or persistent headache. These could be signs of a serious condition.

If pregnant or breast-feeding, ask a health professional before use.

Keep out of reach of children. In case of overdose, get medical help or contact a Poison Control Center right away.

Directions:

Do not take more than 6 doses in any 24-hour period.

Adults & Children 12 years of age and older | Take 4 teaspoons (20 mL) every 4 hours, as needed.
Children 6 to under 12 years of age | Take 2 teaspoons (10 mL) every 4 hours, as needed.
Children 2 to under 6 | Take one pre-measured single dose package (1 teaspoon or 5 mL) every 4 hours, as needed.
Children under 2 years | Do not use.

Other Information:

• Tamper Evident. Do not use if packet is torn, cut or opened.

• Store at controlled room temperature 15° to 30°C (59° to 86°F).

• Avoid excessive heat or humidity.

Inactive Ingredients:

Citric acid, Flavor, Glycerin, Methylparaben, Propylene glycol, Propylparaben, Purified water, Sodium citrate and Sucralose

COUGH SUPPRESSANT, EXPECTORANT, NASAL DECONGESTANT

SUGAR, ALCOHOL, SACCHARIN, SORBITOL & DYE FREE

ORANGE FLAVOR

Manufactured in the USA for: Kramer Novis, San Juan, PR 00917.

1 (787) 767-2072 www.kramernovis.com